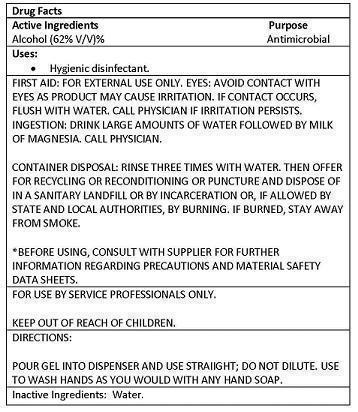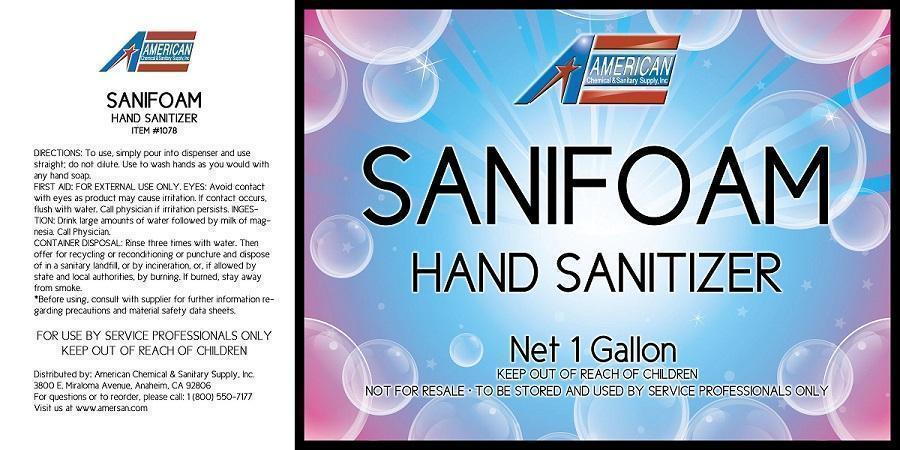 DRUG LABEL: SANIFOAM HAND SANITIZER
NDC: 50536-078 | Form: GEL
Manufacturer: AMERICAN CHEMICAL AND SANITARY SUPPLY INC
Category: otc | Type: HUMAN OTC DRUG LABEL
Date: 20250423

ACTIVE INGREDIENTS: ALCOHOL 62 mL/100 mL
INACTIVE INGREDIENTS: WATER

ACCS (as PLD) - SANIFOAM HAND SANITIZER (50536-078)

ACTIVE INGREDIENT:

ALCOHOL (62% V/V)

PURPOSE:

ANTIMICROBIAL

WARNINGS

FIRST AID:

EYES: AVOID CONTACT WITH EYES. IF CONTACT OCCURS, RINSE WITH WATER. CALL PHYSICIAN IF IRRITATION OR REDNESS DEVELOPS AND LASTS.

INGESTION: IN CASE OF ACCIDENTAL INGESTION, GET MEDICAL OR CONTACT A POISON CNTROL CENTER IMMEDIATELY.

CONTAINER DISPOSAL: RINSE THREE TIMES WITH WATER. THEN OFFER FOR RECYCLING OR RECONDITIONING OR PUNCTURE AND DISPOSE OF IN A SANITARY LANDFILL OR BY INCARCERATION OR, IF ALLOWED BY STATE AND LOCAL AAUTHORITIES, BY BURNING. IF BURNED, STAY AWAY FROM SMOKE.

INDICATIONS AND USAGE

USES: Hygienic disinfectant.

KEEP OUT OF REACH OF CHILDREN

FOR USE BY SERVICE PROFESSIONALS ONLY.

KEEP OUT OF REACH OF CHILDREN.

INACTIVE INGREDIENTS: WATER

DIRECTIONS:

POUR GEL INTO DISPENSER AND USE STRAIIGHT; DO NOT DILUTE. WET HANDS THOROUGHLY WITH PRODUCT AND ALLOW TO DRY WITHOUT WIPING. FOR EXTERNAL USE ONLY.